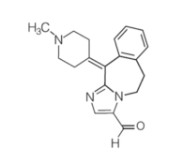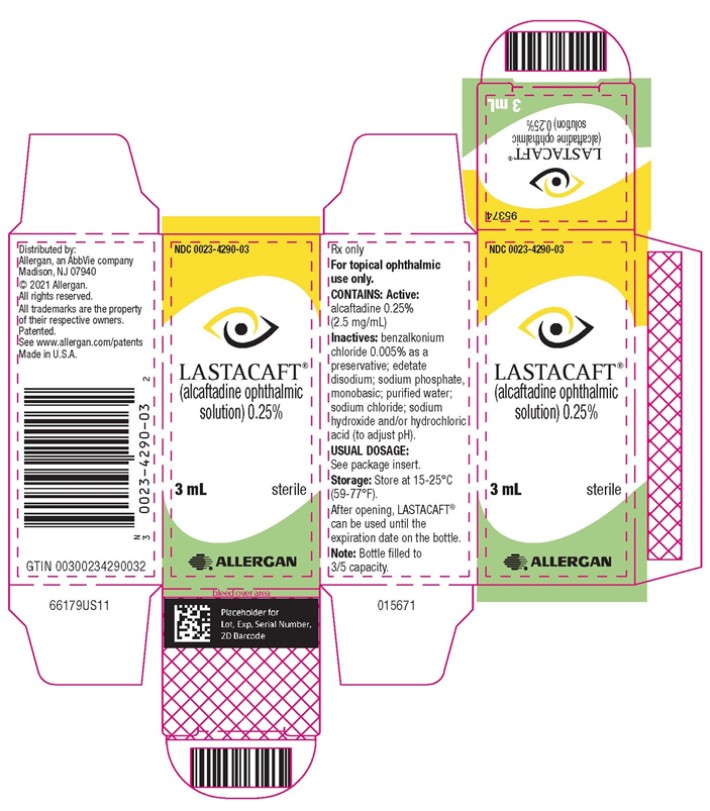 DRUG LABEL: LASTACAFT
NDC: 0023-4290 | Form: SOLUTION/ DROPS
Manufacturer: Allergan, Inc.
Category: prescription | Type: HUMAN PRESCRIPTION DRUG LABEL
Date: 20200601

ACTIVE INGREDIENTS: alcaftadine 2.5 mg/1 mL
INACTIVE INGREDIENTS: BENZALKONIUM CHLORIDE; edetate disodium; sodium phosphate, monobasic; water; sodium chloride; sodium hydroxide; hydrochloric acid

HIGHLIGHTS OF PRESCRIBING INFORMATION

These highlights do not include all the information needed to use LASTACAFT® safely and effectively. See full prescribing information for LASTACAFT®.
LASTACAFT® (alcaftadine ophthalmic solution),
for topical ophthalmic use
Initial U.S. Approval: 2010

1 INDICATIONS AND USAGE

LASTACAFT® is an H1 histamine receptor antagonist indicated for the prevention of itching associated with allergic conjunctivitis. (1)

2 DOSAGE AND ADMINISTRATION

Instill one drop in each eye once daily. (2)

3 DOSAGE FORMS AND STRENGTHS

Ophthalmic solution containing alcaftadine 0.25% (2.5 mg/mL) (3)

4 CONTRAINDICATIONS

Hypersensitivity (4)

5 WARNINGS AND PRECAUTIONS

• Potential for Eye Injury and Contamination: To minimize the risk of eye injury and contamination, do not touch dropper tip to eyelids and surrounding areas, or any other surface. Keep bottle tightly closed when not in use. (5.1)

• Contact Lens Wear: LASTACAFT® should not be used to treat contact lens-related irritation. Remove contact lenses prior to instillation of LASTACAFT®. (5.2)

6 ADVERSE REACTIONS

The most common ocular adverse reactions, occurring in less than 4% of eyes treated with LASTACAFT®, were eye irritation, burning and/or stinging on instillation, eye redness, and eye pruritus. (6.1)

To report SUSPECTED ADVERSE REACTIONS, contact Allergan at 1-800-678-1605 or FDA at 1-800-FDA-1088 or www.fda.gov/medwatch.

FULL PRESCRIBING INFORMATION

1 INDICATIONS AND USAGE

LASTACAFT® is an H1 histamine receptor antagonist indicated for the prevention of itching associated with allergic conjunctivitis.

2 DOSAGE AND ADMINISTRATION

Instill one drop in each eye once daily. If more than 1 topical ophthalmic medicinal product is being used, each one should be administered at least 5 minutes apart.

3 DOSAGE FORMS AND STRENGTHS

Ophthalmic solution containing alcaftadine 0.25% (2.5 mg/mL).

4 CONTRAINDICATIONS

LASTACAFT® is contraindicated in patients with hypersensitivity to any component in the product.

5 WARNINGS AND PRECAUTIONS

5.1 Potential for Eye Injury and Contamination

To minimize eye injury and contamination of the dropper tip and solution, care should be taken not to touch the eyelids or surrounding areas with the dropper tip of the bottle. Keep bottle tightly closed when not in use.

5.2 Contact Lens Use

Patients should be advised not to wear a contact lens if their eye is red.

LASTACAFT® should not be used to treat contact lens-related irritation.

LASTACAFT® should not be instilled while wearing contact lenses. Remove contact lenses prior to instillation of LASTACAFT®. The preservative in LASTACAFT®, benzalkonium chloride, may be absorbed by soft contact lenses. Lenses may be reinserted after 10 minutes following administration of LASTACAFT®.

6 ADVERSE REACTIONS

6.1 Clinical Trials Experience

Because clinical trials are conducted under widely varying conditions, adverse reaction rates observed in the clinical trials of a drug cannot be directly compared to rates in the clinical trials of another drug and may not reflect the rates observed in clinical practice.

The most frequent ocular adverse reactions, occurring in less than 4% of eyes treated with LASTACAFT®, were eye irritation, burning and/or stinging upon instillation, eye redness and eye pruritus.

The most frequent non-ocular adverse reactions, occurring in less than 3% of subjects with eyes treated with LASTACAFT®, were nasopharyngitis and headache. Some of these events were similar to the underlying disease being studied.

6.2 Postmarketing Experience

The following adverse reactions have been identified during post-approval use of LASTACAFT®. Because these reactions are reported voluntarily from a population of uncertain size, it is not always possible to reliably estimate their frequency or establish a causal relationship to drug exposure.

These reactions include eye discharge, eye swelling, erythema of eyelid, eyelid edema, lacrimation increased, vision blurred, hypersensitivity reactions including swelling of the face or allergic dermatitis, and somnolence.

8 USE IN SPECIFIC POPULATIONS

8.1 Pregnancy

Risk Summary

There are no adequate and well-controlled studies with LASTACAFT® in pregnant women to inform a drug associated risk. There are limited data with the use of alcaftadine eye drops in pregnant women.

In embryofetal studies in rats and rabbits, oral administration of alcaftadine during the period of organogenesis did not produce maternal or embryofetal toxicity at clinically relevant doses.

Advise pregnant women of a potential risk to the fetus and mother. LASTACAFT® should only be used during pregnancy if the potential benefit justifies the potential risk to the fetus and mother. The background risk of major birth defects and miscarriage for the indicated population is unknown. However, the background risk in the U.S. general population of major birth defects is 2 to 4%, and of miscarriage is 15 to 20%, of clinically recognized pregnancies.

Data

Animal Data

In rats, oral administration of 5, 20 or 40 mg/kg/day alcaftadine during the period of organogenesis (gestational days 6 – 16) caused maternal lethality at doses of 40 mg/kg. The no observed adverse effect level (NOAEL) for maternal toxicity was 20 mg/kg/day (an exposure 230-times higher than that at the maximum recommended human ophthalmic dose [MRHOD], based on AUC). There were no adverse embryofetal effects up to a dose of 20 mg/kg.

In rabbits, oral administration of 10, 40 or 80 mg/kg/day alcaftadine during the period of organogenesis (gestational days 6 – 18) caused no maternal toxicity or adverse embryofetal effects up to a dose of 80 mg/kg/day (an exposure 8819-times higher than that at the MRHOD, based on AUC).

Daily oral doses of 20 and 30 mg/kg/day alcaftadine administered to rats from Day 6 of pregnancy until Day 20 postpartum produced lower pup weights in offspring. No adverse effects in dams or offspring were observed at doses up to 5 mg/kg/day (a dose 286 times higher than the MRHOD, on a mg/m2 basis).

8.2 Lactation

Risk Summary

There is no information regarding the presence of LASTACAFT® in human milk, the effects on the breastfed infants, or the effects on milk production to inform risk of LASTACAFT® to an infant during lactation. The developmental and health benefits of breastfeeding should be considered, along with the mother’s clinical need for LASTACAFT®, and any potential adverse effects on the breastfed infant from LASTACAFT®.

8.4 Pediatric Use

Safety and effectiveness in pediatric patients below the age of 2 years have not been established.

8.5 Geriatric Use

No overall differences in safety or effectiveness were observed between elderly and younger subjects.

11 DESCRIPTION

LASTACAFT® (alcaftadine ophthalmic solution) is an H1 receptor antagonist, in a sterile ophthalmic solution for topical ophthalmic use.

Alcaftadine is a white to yellow powder with an empirical formula of C19H21N3O and a molecular weight of 307.39.

Contains:

Active: alcaftadine 0.25% (2.5 mg/mL)

Inactives: benzalkonium chloride 0.005% as a preservative; edetate disodium; sodium phosphate, monobasic; purified water; sodium chloride; sodium hydroxide and/or hydrochloric acid (to adjust pH)

Chemical Name: 6,11-dihydro-11-(1-methyl-4-piperidinylidene)-5H-imidazo[2,1-b] [3] benzazepine-3-carboxaldehyde

Structural Formula:

The drug product has a pH of approximately 7 and an osmolality of approximately 290 mOsm/kg.

12 CLINICAL PHARMACOLOGY

12.1 Mechanism of Action

Alcaftadine is an H1 histamine receptor antagonist and inhibitor of the release of histamine from mast cells. Decreased chemotaxis and inhibition of eosinophil activation has also been demonstrated.

12.3 Pharmacokinetics

Absorption

Following bilateral topical ocular administration of alcaftadine ophthalmic solution, 0.25%, the mean plasma Cmax of alcaftadine was approximately 60 pg/mL and the median Tmax occurred at 15 minutes. Plasma concentrations of alcaftadine were below the lower limit of quantification (10 pg/mL) by 3 hours after dosing. The mean Cmax of the active carboxylic acid metabolite was approximately 3 ng/mL and occurred at 1 hour after dosing. Plasma concentrations of the carboxylic acid metabolite were below the lower limit of quantification (100 pg/mL) by 12 hours after dosing. There was no indication of systemic accumulation or changes in plasma exposure of alcaftadine or the active metabolite following daily topical ocular administration.

Distribution

The protein binding of alcaftadine and the active metabolite are 39.2% and 62.7%, respectively.

Elimination

Metabolism

The metabolism of alcaftadine is mediated by non-CYP450 cytosolic enzymes to the active carboxylic acid metabolite. In vitro studies showed that neither alcaftadine nor the carboxylic acid metabolite substantially inhibited reactions catalyzed by major CYP450 enzymes.

Excretion

The elimination half-life of the carboxylic acid metabolite is approximately 2 hours following topical ocular administration. Based on data following oral administration of alcaftadine, the carboxylic acid metabolite is primarily eliminated unchanged in the urine.

13 NONCLINICAL TOXICOLOGY

13.1 Carcinogenesis, Mutagenesis, Impairment of Fertility

Carcinogenesis

The carcinogenic potential of alcaftadine has not been evaluated in long-term animal studies.

Mutagenesis

Alcaftadine was not mutagenic or genotoxic in the Ames test, the mouse lymphoma assay or the mouse micronucleus assay.

Impairment of Fertility

Alcaftadine was found to have no effect on fertility of male and female rats at oral doses up to 20 mg/kg/day (an exposure 230-times higher than that at the MRHOD, based on AUC).

14 CLINICAL STUDIES

Clinical efficacy was evaluated in conjunctival allergen challenge (CAC) studies.
LASTACAFT® was more effective than its vehicle in preventing ocular itching in patients with allergic conjunctivitis induced by an ocular allergen challenge, both at 3 minutes post-dosing and at 16 hours post-dosing of LASTACAFT®.

The safety of LASTACAFT® was evaluated in a randomized clinical study of 909 subjects over a period of 6 weeks.

16 HOW SUPPLIED/STORAGE AND HANDLING

LASTACAFT® (alcaftadine ophthalmic solution) 0.25% is supplied in an opaque, white low-density polyethylene bottle with a white polystyrene cap.

3 mL fill in 5 mL bottle NDC 0023-4290-03

Storage: Store at 15°C to 25°C (59°F to 77°F).

After opening, LASTACAFT® can be used until the expiration date on the bottle.

17 PATIENT COUNSELING INFORMATION

Potential for Eye Injury and Sterility of Dropper Tip

To minimize eye injury and contamination of the dropper tip and solution, advise patients to not touch the eyelids or surrounding areas with the dropper tip, as this may contaminate the contents.

Concomitant Use with other Ophthalmic Products

If more than one topical ophthalmic drug is being used, the drugs should be administered at least five minutes apart.

Contact Lens Use

Advise patients not to wear a contact lens if their eye is red. LASTACAFT® should not be used to treat contact lens-related irritation. Advise patients remove contact lenses prior to instillation of LASTACAFT®. The preservative in LASTACAFT®, benzalkonium chloride, may be absorbed by soft contact lenses. Lenses may be reinserted after 10 minutes following administration of LASTACAFT®.

Distributed by: Allergan, an AbbVie company
Madison, NJ 07940

© 2020 Allergan. All rights reserved.
All trademarks are the property of their respective owners.
Patented. See www.allergan.com/patents

v1.0USPI4290

PRINCIPAL DISPLAY PANEL

NDC 0023-4290-03
LASTACAFT
(alcaftadine
ophthalmic
solution) 0.25%
3 mL
sterile

ALLERGAN